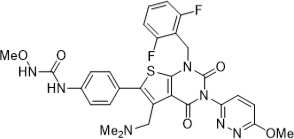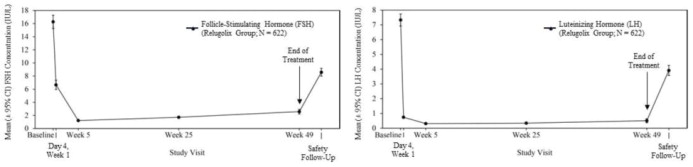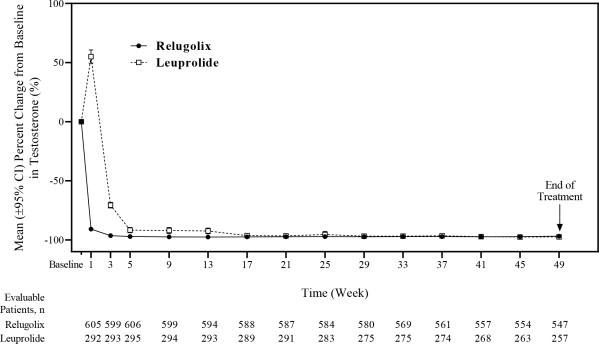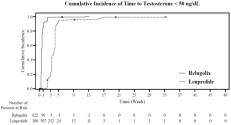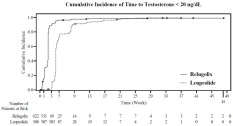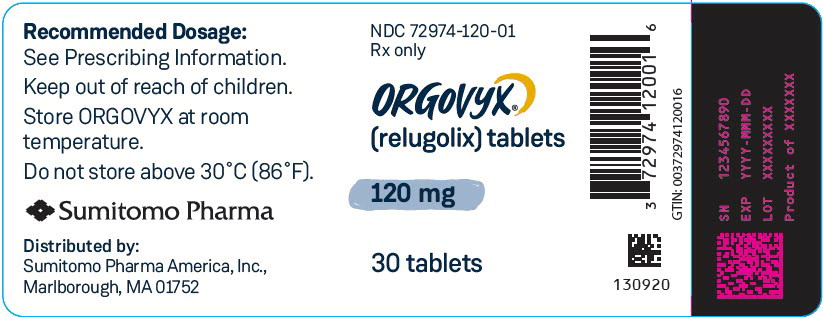 DRUG LABEL: Orgovyx
NDC: 72974-120 | Form: TABLET, FILM COATED
Manufacturer: Sumitomo Pharma America, Inc.
Category: prescription | Type: HUMAN PRESCRIPTION DRUG LABEL
Date: 20251010

ACTIVE INGREDIENTS: relugolix 120 mg/1 1
INACTIVE INGREDIENTS: MANNITOL; SODIUM STARCH GLYCOLATE TYPE A; HYDROXYPROPYL CELLULOSE (90000 WAMW); MAGNESIUM STEARATE; HYPROMELLOSE 2910 (6 MPA.S); TITANIUM DIOXIDE; FERRIC OXIDE RED; CARNAUBA WAX

HIGHLIGHTS OF PRESCRIBING INFORMATION

These highlights do not include all the information needed to use ORGOVYX safely and effectively. See full prescribing information for ORGOVYX.
ORGOVYX (relugolix) tablets, for oral use
Initial U.S. Approval: 2020

1 INDICATIONS AND USAGE

ORGOVYX is a gonadotropin-releasing hormone (GnRH) receptor antagonist indicated for the treatment of adult patients with advanced prostate cancer (1).

2 DOSAGE AND ADMINISTRATION

- Recommended Dosage: A loading dose of 360 mg on the first day of treatment followed by 120 mg taken orally once daily, at approximately the same time each day (2.1).
- ORGOVYX can be taken with or without food (2.1, 12.3). Instruct patients to swallow tablets whole and not to crush or chew tablets (2.1).

3 DOSAGE FORMS AND STRENGTHS

- Tablets: 120 mg (3).

4 CONTRAINDICATIONS

Known severe hypersensitivity to relugolix or to any of the product components (4).

5 WARNINGS AND PRECAUTIONS

- QT/QTc Interval Prolongation: Androgen deprivation therapy may prolong the QT interval (5.1).
- Hypersensitivity: ORGOVYX can cause hypersensitivity reactions, including angioedema. Withhold ORGOVYX in patients who experience symptoms of hypersensitivity. Discontinue ORGOVYX for severe hypersensitivity reactions and manage as clinically indicated (5.2).
- Embryo-Fetal Toxicity: ORGOVYX can cause fetal harm. Advise males with female partners of reproductive potential to use effective contraception (5.3, 8.1, 8.3).

6 ADVERSE REACTIONS

The most common adverse reactions (≥ 10%) and laboratory abnormalities (≥ 15%) were hot flush, glucose increased, triglycerides increased, musculoskeletal pain, hemoglobin decreased, alanine aminotransferase (ALT) increased, fatigue, aspartate aminotransferase (AST) increased, constipation, and diarrhea (6.1).

To report SUSPECTED ADVERSE REACTIONS, contact Sumitomo Pharma America, at 1-833-696-8268 or FDA at 1-800-FDA-1088 or www.fda.gov/medwatch.

7 DRUG INTERACTIONS

P-gp Inhibitors: Avoid co-administration. If unavoidable, take ORGOVYX first, separate dosing by at least 6 hours, and monitor patients more frequently for adverse reactions (2.2, 7.1).

Combined P-gp and Strong CYP3A Inducers: Avoid co-administration. If unavoidable, increase the ORGOVYX dose to 240 mg once daily (2.3, 7.1).

FULL PRESCRIBING INFORMATION

1 INDICATIONS AND USAGE

ORGOVYX is indicated for the treatment of adult patients with advanced prostate cancer.

2 DOSAGE AND ADMINISTRATION

2.1 Recommended Dosage

Initiate treatment of ORGOVYX with a loading dose of 360 mg on the first day and continue treatment with a 120 mg dose taken orally once daily at approximately the same time each day.

ORGOVYX can be taken with or without food [see Clinical Pharmacology (12.3)]. Instruct patients to swallow tablets whole and not to crush or chew tablets.

Advise patients to take a missed dose of ORGOVYX as soon as they remember. If the dose was missed by more than 12 hours, patients should not take the missed dose and resume with the next scheduled dose.

If treatment with ORGOVYX is interrupted for greater than 7 days, restart ORGOVYX with a loading dose of 360 mg on the first day, and continue with a dose of 120 mg once daily.

In patients treated with GnRH receptor agonists and antagonists for prostate cancer, treatment is usually continued upon development of nonmetastatic or metastatic castration-resistant prostate cancer.

2.2 Dosage Modifications for P-gp Inhibitors

Avoid co-administration of ORGOVYX with oral P-gp inhibitors. If co-administration is unavoidable, take ORGOVYX first and separate dosing by at least 6 hours [see Drug Interactions (7.1) and Clinical Pharmacology (12.3)]. Monitor patients for increased adverse reactions.

Treatment with ORGOVYX may be interrupted for up to two weeks if a short course of treatment with a P-gp inhibitor is required. Resume ORGOVYX after the P-gp inhibitor is discontinued. If treatment with ORGOVYX is interrupted for greater than 7 days, restart ORGOVYX with a loading dose of 360 mg on the first day and continue with a dose of 120 mg once daily.

2.3 Dosage Modifications for Combined P-gp and Strong CYP3A Inducers

Avoid co-administration of ORGOVYX with combined P-gp and strong CYP3A inducers. If co-administration is unavoidable, increase the ORGOVYX dose to 240 mg once daily. After discontinuation of the combined P-gp and strong CYP3A inducer, resume the recommended ORGOVYX dose of 120 mg once daily [see Drug Interactions (7.1) and Clinical Pharmacology (12.3)].

3 DOSAGE FORMS AND STRENGTHS

Tablets: 120 mg, light red, almond-shaped, film-coated, and debossed with “R” on one side and “120” on the other side.

4 CONTRAINDICATIONS

ORGOVYX is contraindicated in patients with severe hypersensitivity to relugolix or to any of the product components.

5 WARNINGS AND PRECAUTIONS

5.1 QT/QTc Interval Prolongation

Androgen deprivation therapy, such as ORGOVYX, may prolong the QT/QTc interval. Providers should consider whether the benefits of androgen deprivation therapy outweigh the potential risks in patients with congenital long QT syndrome, congestive heart failure, or frequent electrolyte abnormalities and in patients taking drugs known to prolong the QT interval. Electrolyte abnormalities should be corrected. Consider periodic monitoring of electrocardiograms and electrolytes [see Clinical Pharmacology (12.2)].

5.2 Hypersensitivity Reactions

ORGOVYX is contraindicated in patients with severe hypersensitivity to relugolix or any of the product components [see Contraindications (4)]. Hypersensitivity reactions, including pharyngeal edema and other serious cases of angioedema, have been reported postmarketing in patients treated with ORGOVYX.

In HERO, patients treated with relugolix reported angioedema (0.2%) [see Clinical Trials Experience (6.1)].

Advise patients who experience any symptoms of hypersensitivity to temporarily discontinue ORGOVYX and promptly seek medical care.

Discontinue ORGOVYX for severe hypersensitivity reactions and manage as clinically indicated.

5.3 Embryo-Fetal Toxicity

The safety and efficacy of ORGOVYX have not been established in females. Based on findings in animals and mechanism of action, ORGOVYX can cause fetal harm and loss of pregnancy when administered to a pregnant female. In an animal reproduction study, oral administration of relugolix to pregnant rabbits during the period of organogenesis caused embryo-fetal lethality at maternal exposures that were 0.3 times the human exposure at the recommended dose of 120 mg daily based on area under the curve (AUC). Advise males with female partners of reproductive potential to use effective contraception during treatment and for 2 weeks after the last dose of ORGOVYX [see Use in Specific Populations (8.1, 8.3) and Clinical Pharmacology (12.1)].

5.4 Laboratory Testing

Therapy with ORGOVYX results in suppression of the pituitary gonadal system. Results of diagnostic tests of the pituitary gonadotropic and gonadal functions conducted during and after ORGOVYX may be affected. The therapeutic effect of ORGOVYX should be monitored by measuring serum concentrations of prostate specific antigen (PSA) periodically. If PSA increases, serum concentrations of testosterone should be measured.

6 ADVERSE REACTIONS

The following clinically significant adverse reactions are described elsewhere in the labeling:

- QT/QTc Interval Prolongation [see Warnings and Precautions (5.1)].

6.1 Clinical Trials Experience

Because clinical trials are conducted under widely varying conditions, adverse reaction rates observed in the clinical trials of a drug cannot be directly compared to rates in the clinical trials of another drug and may not reflect the rates observed in practice.

The safety of ORGOVYX was evaluated in HERO, a randomized (2:1), open-label, clinical study in patients with advanced prostate cancer [see Clinical Studies (14)]. Patients received orally administered ORGOVYX as a loading dose of 360 mg on the first day followed by 120 mg taken orally once daily (n = 622) or received leuprolide acetate administered by depot injection at doses of 22.5 mg (n = 264) or 11.25 mg (n = 44) per local guidelines every 12 weeks (n = 308). Leuprolide acetate 11.25 mg is a dosing regimen that is not recommended for this indication in the US. Among patients who received ORGOVYX, 91% were exposed for at least 48 weeks. Ninety-nine (16%) patients received concomitant radiotherapy and 17 (3%) patients received concomitant enzalutamide with ORGOVYX.

Serious adverse reactions occurred in 12% of patients receiving ORGOVYX. Serious adverse reactions in ≥ 0.5% of patients included myocardial infarction (0.8%), acute kidney injury (0.6%), arrhythmia (0.6%), hemorrhage (0.6%), and urinary tract infection (0.5%). Fatal adverse reactions occurred in 0.8% of patients receiving ORGOVYX including metastatic lung cancer (0.3%), myocardial infarction (0.3%), and acute kidney injury (0.2%). Fatal and non-fatal myocardial infarction and stroke were reported in 2.7% of patients receiving ORGOVYX.

Permanent discontinuation of ORGOVYX due to an adverse reaction occurred in 3.5% of patients. Adverse reactions which resulted in permanent discontinuation of ORGOVYX in ≥ 0.3 % of patients included atrioventricular block (0.3%), cardiac failure (0.3%), hemorrhage (0.3%), increased transaminases (0.3%), abdominal pain (0.3%), and pneumonia (0.3%).

Dosage interruptions of ORGOVYX due to an adverse reaction occurred in 2.7% of patients. Adverse reactions which required dosage interruption in ≥ 0.3% of patients included fracture (0.3%).

The most common adverse reactions (≥ 10%) and laboratory abnormalities (≥ 15%) were hot flush (54%), glucose increased (44%), triglycerides increased (35%), musculoskeletal pain (30%), hemoglobin decreased (28%), alanine aminotransferase increased (ALT) (27%), fatigue (26%), aspartate aminotransferase increased (AST) (18%), constipation (12%), and diarrhea (12%).

Table 1 summarizes the adverse reactions in HERO.

Table 1: Adverse Reactions (≥ 10%) of Patients with Advanced Prostate Cancer Who Received ORGOVYX in HERO
Adverse Reaction | ORGOVYX N = 622 |  | Leuprolide Acetate N = 308
Adverse Reaction | All Grades (%) | Grade 3-4 (%) | All Grades (%) | Grade 3-4 (%)
Vascular disorders
Hot flush | 54 | 0.6 | 52 | 0
Musculoskeletal and connective tissue disorders
Musculoskeletal paina | 30 | 1.1 | 29 | 1.6
General
Fatigueb | 26 | 0.3 | 24 | 0
Gastrointestinal disorders
Diarrheac | 12 | 0.2 | 7 | 0
Constipation | 12 | 0 | 10 | 0
a Includes arthralgia, back pain, pain in extremity, musculoskeletal pain, myalgia, bone pain, neck pain, arthritis, musculoskeletal stiffness, non-cardiac chest pain, musculoskeletal chest pain, spinal pain, and musculoskeletal discomfort.
b Includes fatigue and asthenia.
c Includes diarrhea and colitis.

Clinically relevant adverse reactions in < 10% of patients who received ORGOVYX included increased weight, insomnia, gynecomastia, hyperhidrosis, depression, decreased libido, and angioedema.

Table 2 summarizes the laboratory abnormalities in HERO.

Table 2: Select Laboratory Abnormalities (≥ 15%) That Worsened from Baseline in Patients with Advanced Prostate Cancer Who Received ORGOVYX in HERO
Laboratory Test | ORGOVYXa |  | Leuprolide Acetatea
Laboratory Test | All Grades (%) | Grade 3-4 (%) | All Grades (%) | Grade 3-4 (%)
Chemistry
Glucose increased | 44 | 2.9 | 54 | 6
Triglycerides increased | 35 | 2 | 36 | 0.7
ALT increased | 27 | 0.3 | 28 | 0
AST increased | 18 | 0 | 19 | 0.3
Hematology
Hemoglobin decreased | 28 | 0.5 | 29 | 0.7
a The denominator used to calculate the rate varied from 611 to 619 in the ORGOVYX arm and from 301 to 306 in the leuprolide arm based on the number of patients with a baseline value and at least one post-treatment value.

6.2 Postmarketing Experience

The following adverse reactions have been identified during post-approval use of ORGOVYX. Because these reactions are reported voluntarily from a population of uncertain size, it is not always possible to reliably estimate their frequency or establish a causal relationship to drug exposure.

Immune system disorders: hypersensitivity, including angioedema and urticaria.

7 DRUG INTERACTIONS

7.1 Effect of Other Drugs on ORGOVYX

P-gp Inhibitors

Relugolix is a P-gp substrate. Co-administration of ORGOVYX with an oral P-gp inhibitor increases relugolix exposure [see Clinical Pharmacology (12.3)], which may increase the risk of adverse reactions associated with ORGOVYX.

Avoid co-administration of ORGOVYX with oral P-gp inhibitors.

If co-administration with an oral P-gp inhibitor cannot be avoided, take ORGOVYX first and separate dosing by at least 6 hours. Monitor patients for increased adverse reactions [see Dosage and Administration (2.2)].

Treatment with ORGOVYX may be interrupted for up to two weeks if a short course of treatment with a P-gp inhibitor is required. Resume ORGOVYX after the P-gp inhibitor is discontinued. If treatment with ORGOVYX is interrupted for greater than 7 days, restart ORGOVYX with a loading dose of 360 mg on the first day and continue with a dose of 120 mg once daily.

Combined P-gp and Strong CYP3A Inducers

Relugolix is a P-gp and CYP3A substrate. Co-administration of ORGOVYX with a combined P-gp and strong CYP3A inducer decreases relugolix exposure, which may reduce the effects of ORGOVYX [see Clinical Pharmacology (12.3)].

Avoid co-administration of ORGOVYX with combined P-gp and strong CYP3A inducers.

If co-administration cannot be avoided, increase the ORGOVYX dose. After discontinuation of the combined P-gp and strong CYP3A inducer, resume ORGOVYX once daily at the same dose [see Dosage and Administration (2.3)].

8 USE IN SPECIFIC POPULATIONS

8.1 Pregnancy

Risk Summary

The safety and efficacy of ORGOVYX have not been established in females. Based on findings in animals and mechanism of action, ORGOVYX can cause fetal harm and loss of pregnancy when administered to a pregnant female [see Clinical Pharmacology (12.1)]. There are no human data on the use of ORGOVYX in pregnant females to inform the drug-associated risk. In an animal reproduction study, oral administration of relugolix to pregnant rabbits during organogenesis caused embryo-fetal lethality at maternal exposures that were 0.3 times the human exposure at the recommended dose of 120 mg daily based on AUC (see Data). Advise patients of the potential risk to the fetus.

Data

Animal Data

In an embryo-fetal development study, oral administration of relugolix to pregnant rabbits during the period of organogenesis resulted in abortion, total litter loss, or decreased number of live fetuses at a dose of 9 mg/kg/day (approximately 0.3 times the human exposure at the recommended dose of 120 mg daily based on AUC).

8.2 Lactation

Risk Summary

The safety and efficacy of ORGOVYX have not been established in females.

Relugolix was detected in human breast milk (see Data). There are no data on the effects of relugolix or its metabolites on the breastfed child, or the effects on milk production.

Data

In a milk-only lactation study in 8 healthy adult lactating women, the mean total amount of relugolix recovered in human breast milk over the first 24 hours was 0.003 mg and over 120 hours (5 days) was 0.004 mg following a single, oral, maternal dose of 40 mg. The mean calculated daily infant dose was 0.0006 mg/kg/day using 0.003 mg (the amount recovered in human breast milk over the first 24 hours). The relative infant dose was 0.1% of the maternal weight-adjusted dose of 40 mg.

8.3 Females and Males of Reproductive Potential

Contraception

Males

Based on findings in animals and mechanism of action, advise male patients with female partners of reproductive potential to use effective contraception during treatment and for 2 weeks after the last dose of ORGOVYX [see Use in Specific Populations (8.1)].

Infertility

Males

Based on findings in animals and mechanism of action, ORGOVYX may impair fertility in males of reproductive potential [see Clinical Pharmacology (12.1) and Nonclinical Toxicology (13.1)].

8.4 Pediatric Use

The safety and efficacy of ORGOVYX in pediatric patients have not been established.

8.5 Geriatric Use

Of the 622 patients who received ORGOVYX in the HERO study, 81% were 65 years of age or older, while 35% were 75 years of age or older. No overall differences in safety or effectiveness were observed between these subjects and younger subjects. There was no clinically relevant impact of age on the pharmacokinetics of ORGOVYX or testosterone response based on population pharmacokinetic and pharmacokinetic/pharmacodynamic analyses in men 45 to 91 years of age.

11 DESCRIPTION

Relugolix is a nonpeptide small molecule, GnRH receptor antagonist. The chemical name is N-(4-{1-[(2,6-difluorophenyl)methyl]-5-[(dimethylamino)methyl]-3-(6-methoxypyridazin-3-yl)-2,4-dioxo-1,2,3,4-tetrahydrothieno[2,3-d]pyrimidin-6-yl}phenyl)-N'-methoxyurea.

The molecular weight is 623.63 daltons and the molecular formula is C29H27F2N7O5S. The structural formula is:

Relugolix is a white to off-white to slightly yellow solid with a solubility of 0.04 mg per mL in water at 25°C.

ORGOVYX is provided as film-coated tablets for oral administration. Each tablet contains 120 mg of relugolix. The inactive ingredients are mannitol, sodium starch glycolate, hydroxypropyl cellulose, magnesium stearate, hypromellose, titanium dioxide, ferric oxide red, and carnauba wax.

12 CLINICAL PHARMACOLOGY

12.1 Mechanism of Action

Relugolix is a nonpeptide GnRH receptor antagonist that competitively binds to pituitary GnRH receptors, thereby, reducing the release of luteinizing hormone (LH) and follicle-stimulating hormone (FSH), and consequently testosterone.

12.2 Pharmacodynamics

Pituitary and Gonadal Hormones

Relugolix reduced LH, FSH (Figure 1), and testosterone concentrations after oral administration of the recommended loading dose of 360 mg and a 120 mg dose once daily.

Out of 622 patients, 56% had testosterone concentrations at castrate levels (< 50 ng/dL) by the first sampling timepoint at Day 4, and 97% maintained castrate levels of testosterone through 48 weeks. In a substudy of 137 patients who did not receive subsequent androgen deprivation therapy for at least 90 days after discontinuation of relugolix, the cumulative incidence rate of achieving testosterone concentrations above the lower limit of the normal range (> 280 ng/dL) or baseline at 90 days was 55% [see Clinical Studies (14)].

Figure 1: Mean (± 95% CI) Follicle-Stimulating Hormone and Luteinizing Hormone Concentrations over Time in HERO

Cardiac Electrophysiology

At a single 60 mg or 360 mg relugolix dose (0.17 or 1 times the recommended loading dose, respectively), clinically significant QTc interval prolongation was not observed.

12.3 Pharmacokinetics

After administration of single doses ranging from 60 mg to 360 mg (0.17 to 1 times the recommended loading dose), total systemic exposure (AUC) and the maximum concentration (Cmax) of relugolix increases in an approximately dose proportional manner. After administration of multiple doses of relugolix once daily, the AUC of relugolix increases in an approximately dose proportional manner while the Cmax increase is greater than dose proportional for doses from 20 mg to 180 mg (0.17 to 1.5 times the recommended daily dose).

After administration of a single 360 mg loading dose, the mean (± standard deviation [± SD]) AUC and Cmax of relugolix are 985 (± 742) ng.hr/mL and 215 (± 184) ng/mL, respectively. After administration of 120 mg once daily, the mean (± SD) AUC and Cmax of relugolix at steady-state are 407 (± 168) ng.hr/mL and 70 (± 65) ng/mL, respectively. The accumulation of relugolix upon once daily administration is approximately 2-fold.

Absorption

Relugolix is a substrate for intestinal P-gp. The mean (CV%) absolute bioavailability of relugolix is 12% (62%). The median (min, max) time to maximum concentration (Tmax) of relugolix is 2.25 (0.5, 5.0) hours.

Effect of Food

No clinically significant differences in the pharmacokinetics of relugolix were observed following administration of a high-calorie, high-fat meal (approximately 800 to 1000 calories with 500, 220, and 124 from fat, carbohydrate, and protein, respectively).

Distribution

Plasma protein binding of relugolix is 68 to 71%, primarily to albumin and to a lesser extent to α1-acid glycoprotein. The mean blood-to-plasma ratio is 0.78.

Elimination

The mean effective half-life of relugolix is 25 hours and the mean (CV%) terminal elimination half-life is 61 (11%) hours. The mean (CV%) total clearance of relugolix is 29 (15%) L/h and the renal clearance is 8 L/h.

Metabolism

Relugolix is metabolized primarily by CYP3A and to a lesser extent by CYP2C8.

Excretion

After oral administration of a single 80 mg radiolabeled dose of relugolix, approximately 81% of the radioactivity was recovered in feces with 4.2% as unchanged and 4.1% in urine with 2.2% as unchanged.

Specific Populations

No clinically significant differences in the pharmacokinetics of relugolix were observed based on age (45 to 91 years), race/ethnicity (Asian [19%], White [71%], Black/African American [6%]), body weight (41 to 193 kg), mild to severe renal impairment (creatinine clearance [CLcr] 15 to 89 mL/min, as estimated by the Cockcroft-Gault equation), or mild to moderate hepatic impairment (Child-Pugh A or B). The effect of end-stage renal disease with or without hemodialysis or severe hepatic impairment (Child-Pugh C) on the pharmacokinetics of relugolix has not been evaluated.

Drug Interactions Studies

Clinical Studies

Combined P-gp and Moderate CYP3A Inhibitors: Co-administration with erythromycin (P-gp and moderate CYP3A inhibitor) increased the AUC and Cmax of relugolix by 3.5- and 2.9-fold respectively.

Combined P-gp and Strong CYP3A Inducers: Co-administration of relugolix with rifampin (P-gp and strong CYP3A inducer) decreased the AUC and Cmax of relugolix by 55% and 23%, respectively.

Other Drugs: No clinically significant differences in the pharmacokinetics of relugolix were observed when co-administered with voriconazole (strong CYP3A inhibitor), atorvastatin, enzalutamide, or acid-reducing agents. No clinically significant differences in the pharmacokinetics of midazolam (sensitive CYP3A substrate) or rosuvastatin (BCRP substrate), or dabigatran etexilate (P-gp substrate) were observed upon co-administration with relugolix.

In Vitro Studies

Cytochrome P450 (CYP) Enzymes: Relugolix is not an inhibitor of CYP1A2, CYP2B6, CYP2C8, CYP2C9, CYP2C19, CYP2D6, or CYP3A4. Relugolix is an inducer of CYP3A and CYP2B6, but not an inducer of CYP1A2.

Transporter Systems: Relugolix is a substrate of P-gp, but not a substrate of BCRP. Relugolix is an inhibitor of BCRP and P-gp, but not an inhibitor of OATP1B1, OATP1B3, OATP2B1, OAT1, OAT3, OCT2, MATE1, MATE2-K, or BSEP.

13 NONCLINICAL TOXICOLOGY

13.1 Carcinogenesis, Mutagenesis, Impairment of Fertility

Two-year carcinogenicity studies were conducted in mice at oral relugolix doses up to 100 mg/kg/day and in rats at doses up to 600 mg/kg/day. Relugolix was not carcinogenic in mice or rats at exposures up to approximately 75 or 224 times, respectively, the human exposure at the recommended dose of 120 mg daily based on AUC.

Relugolix was not mutagenic in the in vitro bacterial reverse mutation (Ames) assay or clastogenic in the in vitro chromosomal aberration assay in Chinese hamster lung cells or the in vivo rat bone marrow micronucleus assay.

In human GnRH-receptor knock-in male mice, oral administration of relugolix decreased prostate and seminal vesicle weights at doses ≥ 3 mg/kg twice daily for 28 days. The effects of relugolix were reversible, except for testis weight, which did not fully recover within 28 days after drug withdrawal. In a 39-week repeat-dose toxicity study in monkeys, there were no significant effects on male reproductive organs at oral relugolix doses up to 50 mg/kg/day (approximately 53 times the human exposure at the recommended dose of 120 mg daily based on AUC).

13.2 Animal Toxicology and/or Pharmacology

Phospholipidosis (intracellular phospholipid accumulation) was observed in multiple organs and tissues (e.g., liver, pancreas, spleen, kidney, lymph nodes, lung, bone marrow, gastrointestinal tract or testes) after repeated oral administration of relugolix in rats and monkeys. In a rat 26-week toxicity study, phospholipidosis was observed at doses ≥ 100 mg/kg (approximately 18 times the human exposure at the recommended dose based on AUC). In a monkey 39-week toxicity study, this effect was observed at doses ≥ 1.5 mg/kg (approximately 0.6 times the human exposure at the recommended dose based on AUC) and demonstrated evidence of reversibility after cessation of treatment. The significance of this finding in humans is unknown.

14 CLINICAL STUDIES

HERO Study

The safety and efficacy of ORGOVYX was evaluated in HERO (NCT03085095), a randomized, open label study in men with advanced prostate cancer requiring at least 1 year of androgen deprivation therapy and defined as biochemical (PSA) or clinical relapse following local primary intervention, newly diagnosed castration-sensitive metastatic disease, or advanced localized disease.

A total of 934 patients were randomized to receive ORGOVYX or leuprolide in a 2:1 ratio for 48 weeks:

a) ORGOVYX at a loading dose of 360 mg on the first day followed by daily doses of 120 mg orally.
b) Leuprolide acetate 22.5 mg injection (or 11.25 mg in Japan and Taiwan) subcutaneously every 3 months. Leuprolide acetate 11.25 mg is a dosage regimen that is not recommended for this indication in the US.

Serum testosterone concentrations were measured at screening; on Days 1, 4, 8, 15, and 29 in the first month; then monthly until the end of the study.

The population (N = 930) across both treatment groups had a median age of 71 years (range 47 to 97 years). The ethnic/racial distribution was 68% White, 21% Asian, 4.9% Black, and 5% other. Disease stage was distributed as follows: 32% metastatic (M1), 31% locally advanced (T3/4 NX M0 or any T N1 M0), 28% localized (T1 or T2 N0 M0), and 10% not classifiable. The median testosterone concentration at baseline across the treatment groups was 408 ng/dL.

The major efficacy outcome measure was medical castration rate defined as achieving and maintaining serum testosterone suppression to castrate levels (< 50 ng/dL) by Day 29 through 48 weeks of treatment. Other endpoints included castration rates on Day 4 and 15 and castration rates with testosterone < 20 ng/dL at Day 15.

The efficacy results are shown in Table 3 and the time course of percent change from baseline in testosterone suppression by ORGOVYX and leuprolide during the 48 week treatment period are shown in Figure 2.

Table 3: Medical Castration Rates (Testosterone Concentrations < 50 ng/dL) from Day 29 through Week 48 in HERO
 | ORGOVYX 360/120 mg (N = 622) b | Leuprolide Acetate 22.5 or 11.25 mga (N = 308) b
Castration Rate (95% CI)c | 96.7% (94.9%, 97.9%) | 88.8% (84.6%, 91.8%)
a 11.25 mg is a dosage regimen that is not recommended for this indication in the US. The castration rate of the subgroup of patients receiving 22.5 mg leuprolide (n = 264) was 88.0% (95% CI: 83.4%, 91.4%).
b Two patients in each arm did not receive the study treatment and were not included.
c Kaplan-Meier estimates within group.

Figure 2: Mean (95% CI) Percent Change from Baseline in Testosterone Concentrations from Baseline to Week 49 by Treatment Group in HERO

The percentages of patients who attained the medical castration levels of testosterone < 50 ng/dL and < 20 ng/dL within the first 29 days of treatment are summarized in Table 4 and the cumulative incidences of time to testosterone < 50 ng/dL or < 20 ng/dL are shown in Figure 3.

Table 4: Percentage of Patients Attaining Testosterone Decreases within the First 29 Days in HEROa
 | Testosterone < 50 ng/dL |  | Testosterone < 20 ng/dL
 | ORGOVYX (N = 622) | Leuprolide Acetate (N = 308) | ORGOVYX (N = 622) | Leuprolide Acetate (N = 308)
Day 4 | 56% | 0% | 7% | 0%
Day 8 | 91% | 0% | 27% | 0%
Day 15 | 99% | 12% | 78% | 1%
Day 29 | 99% | 82% | 95% | 57%
a Kaplan-Meier estimates within group.

Figure 3: Cumulative Incidence of Time to Testosterone < 50 ng/dL and < 20 ng/dL in HERO

In the clinical trial, PSA levels were monitored and were lowered on average by 65% two weeks after administration of ORGOVYX, 83% after 4 weeks, 92% after 3 months and remained suppressed throughout the 48 weeks of treatment. These PSA results should be interpreted with caution because of the heterogeneity of the patient population studied. No evidence has shown that the rapidity of PSA decline is related to a clinical benefit.

A substudy was conducted in 137 patients who did not receive subsequent androgen deprivation therapy for at least 90 days after discontinuation of ORGOVYX. Based on Kaplan-Meier analyses, 55% of patients achieved testosterone levels above the lower limit of the normal range (> 280 ng/dL) or baseline at 90 days after discontinuation of ORGOVYX.

16 HOW SUPPLIED/STORAGE AND HANDLING

How Supplied

The 120 mg tablets are film-coated, light red, almond shaped, and debossed with “R” on one side and “120” on the other side and are supplied in two configurations, bottles and blister packs. Each bottle (NDC 72974-120-01) contains 30 tablets and a desiccant and is closed with a child resistant induction seal cap. The blister cards contain nine tablets packaged in a carton (NDC 72974-120-02). Each ORGOVYX tablet contains 120 mg of relugolix.

Storage and Handling

- Store ORGOVYX at room temperature. Do not store above 30°C (86°F).
- Dispense to patients in original container only.
- For bottles, keep container tightly closed after first opening.
- Keep out of reach of children.

17 PATIENT COUNSELING INFORMATION

Advise the patient to read the FDA-approved patient labeling (Patient Information).

QT/QTc Interval Prolongation

- Advise patients that androgen deprivation therapy treatment with ORGOVYX may prolong the QT interval. Inform patients of the signs and symptoms of QT prolongation. Advise patients to contact their healthcare provider immediately for signs or symptoms of QT prolongation [see Warnings and Precautions (5.1)].

Hypersensitivity

- Inform patients that if they have experienced severe hypersensitivity with relugolix or to any of the product components, ORGOVYX is contraindicated [see Contraindications (4)].
- Inform patients that ORGOVYX can cause severe hypersensitivity reactions that include angioedema [see Warnings and Precautions (5.2)].
- Advise patients who experience hypersensitivity symptoms to discontinue ORGOVYX and promptly contact their healthcare provider.

Androgen Deprivation

- Inform patients about adverse reactions related to androgen deprivation therapy with ORGOVYX, including hot flashes, flushing of the skin, increased weight, decreased sex drive, and difficulties with erectile function [see Adverse Reactions (6.1)].

Embryo-Fetal Toxicity

- Inform patients that ORGOVYX can be harmful to a developing fetus and can cause loss of pregnancy.
- Advise male patients with female partners of reproductive potential to use effective contraception during treatment and for 2 weeks after the last dose of ORGOVYX [see Warnings and Precautions (5.3) and Use in Specific Populations (8.1, 8.3)].

Infertility

- Inform patients that ORGOVYX may cause infertility [see Use in Specific Populations (8.3)].

Drug Disposal

- Advise patients to dispose of unused medication via a take-back option if available. Otherwise, advise to follow FDA instructions for disposing medication in the household trash, www.fda.gov/drugdisposal and NOT to flush down the toilet.

Manufactured for Sumitomo Pharma America, Inc., Marlborough, MA 01752

214621-MS-006

PATIENT INFORMATION
ORGOVYX (or-GO-vix)
(relugolix)
Tablets

What is ORGOVYX?
ORGOVYX is a prescription medicine used in adults for the treatment of advanced prostate cancer.
It is not known if ORGOVYX is safe or effective in females.
It is not known if ORGOVYX is safe or effective in children.

Do not take ORGOVYX if you have had a severe allergic reaction to relugolix or any of the ingredients in ORGOVYX. See the end of this Patient Information for a complete list of the ingredients in ORGOVYX.

Before taking ORGOVYX, tell your healthcare provider about all of your medical conditions, including if you:

- have any heart problems, including a condition called long QT syndrome.
- are pregnant or plan to become pregnant. ORGOVYX can harm your unborn baby and cause loss of pregnancy (miscarriage).
- have a partner who is pregnant or may become pregnant.
  - Males who have female partners who are able to become pregnant should use effective birth control (contraception) during treatment with ORGOVYX and for 2 weeks after the last dose of ORGOVYX.
- are breastfeeding or plan to breastfeed. It is not known if ORGOVYX passes into your breast milk.

Tell your healthcare provider about all the medicines you take, including prescription and over-the-counter medicines, vitamins, and herbal supplements. Taking ORGOVYX with certain other medicines can affect how ORGOVYX works or may cause side effects.
You should not start or stop any medicine before you talk with your healthcare provider who prescribed ORGOVYX.
Know the medicines you take. Keep a list of them with you to show to your healthcare provider and pharmacist when you get a new medicine.

How should I take ORGOVYX?

- Take ORGOVYX exactly as your healthcare provider tells you.
- Take 3 ORGOVYX tablets on your first day of treatment. After that, take 1 ORGOVYX tablet each day.
- Take ORGOVYX at about the same time each day.
- Take ORGOVYX with or without food.
- Swallow ORGOVYX tablets whole. Do not crush or chew tablets.
- Your healthcare provider may change your dose if needed.
- Do not change your dose or stop taking ORGOVYX without talking with your healthcare provider first.
- If you miss a dose of ORGOVYX, take it as soon as you remember. If the dose was missed by more than 12 hours, the missed dose should not be taken. Take your next dose at your regular time the next day.

What are the possible side effects of ORGOVYX?
ORGOVYX may cause serious side effects, including:

- Changes in the electrical activity of your heart (QT prolongation). Your healthcare provider may check your body salts (electrolytes) and the electrical activity of your heart during treatment with ORGOVYX. Tell your healthcare provider right away if you get any signs or symptoms of QT prolongation, including:
  - dizziness
  - fainting
  - feeling that your heart is pounding or racing (palpitations)
  - chest pain
- Allergic reactions. Stop taking ORGOVYX and tell your healthcare provider or get emergency medical help right away if you get any signs or symptoms of an allergic reaction, including:
  - swelling of your face, lips, tongue, throat, or trouble swallowing
  - trouble breathing
  - hives (raised bumps), rash, or redness all over your body

The most common side effects of ORGOVYX include:

- hot flushes
- increased blood sugar levels
- increased blood fat (triglyceride) levels
- muscle and joint pain
- decreased blood hemoglobin levels

- increased liver enzymes
- tiredness
- constipation
- diarrhea

Other side effects include weight gain, decreased sex drive, and erectile function problems.
ORGOVYX may cause fertility problems in males, which may affect your ability to father children. Talk to your healthcare provider if this is a concern for you.
These are not all the possible side effects of ORGOVYX.
Call your doctor for medical advice about side effects. You may report side effects to FDA at 1-800-FDA-1088.

How should I store ORGOVYX?

- Store ORGOVYX at room temperature. Do not store ORGOVYX above 86°F (30°C).
- Keep the bottle tightly closed after you first open it.
- The ORGOVYX bottle contains a desiccant to help keep your medicine dry (protect it from moisture). Do not remove the desiccant from the bottle.
- Dispose of unused medicines through community take-back disposal programs when available. If no community take-back disposal program is available go to www.fda.gov/drugdisposal for information on how to dispose of ORGOVYX the right way.
- Do not flush ORGOVYX down the toilet.

Keep ORGOVYX and all medicines out of the reach of children.

General information about the safe and effective use of ORGOVYX.
Medicines are sometimes prescribed for purposes other than those listed in a Patient Information leaflet. Do not use ORGOVYX for a condition for which it was not prescribed. Do not give ORGOVYX to other people, even if they have the same symptoms that you have. It may harm them. You can ask your pharmacist or healthcare provider for information about ORGOVYX that is written for health professionals.

What are the ingredients in ORGOVYX?
Active ingredient: relugolix
Inactive ingredients: mannitol, sodium starch glycolate, hydroxypropyl cellulose, magnesium stearate, hypromellose, titanium dioxide, ferric oxide red, and carnauba wax.
Manufactured for: Sumitomo Pharma America, Inc., Marlborough, MA 01752
For more information, go to www.orgovyx.com or call 1-833-696-8268.

This Patient Information has been approved by the U.S. Food and Drug Administration.

Revised: 08/2023

214621-MS-005

PRINCIPAL DISPLAY PANEL - 120 mg Tablet Bottle Label

NDC 72974-120-01
Rx only

ORGOVYX®
(relugolix) tablets

120 mg

30 tablets